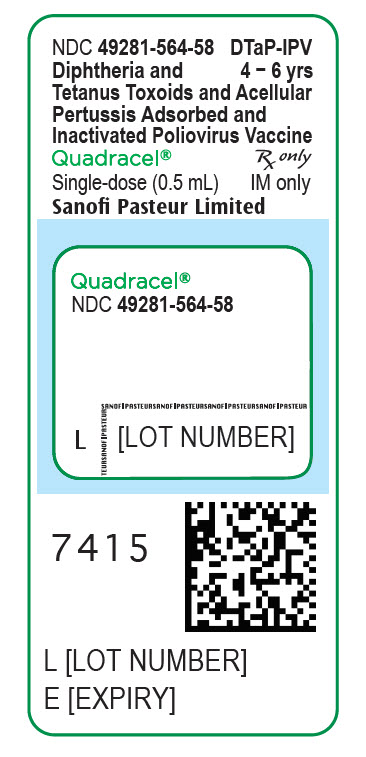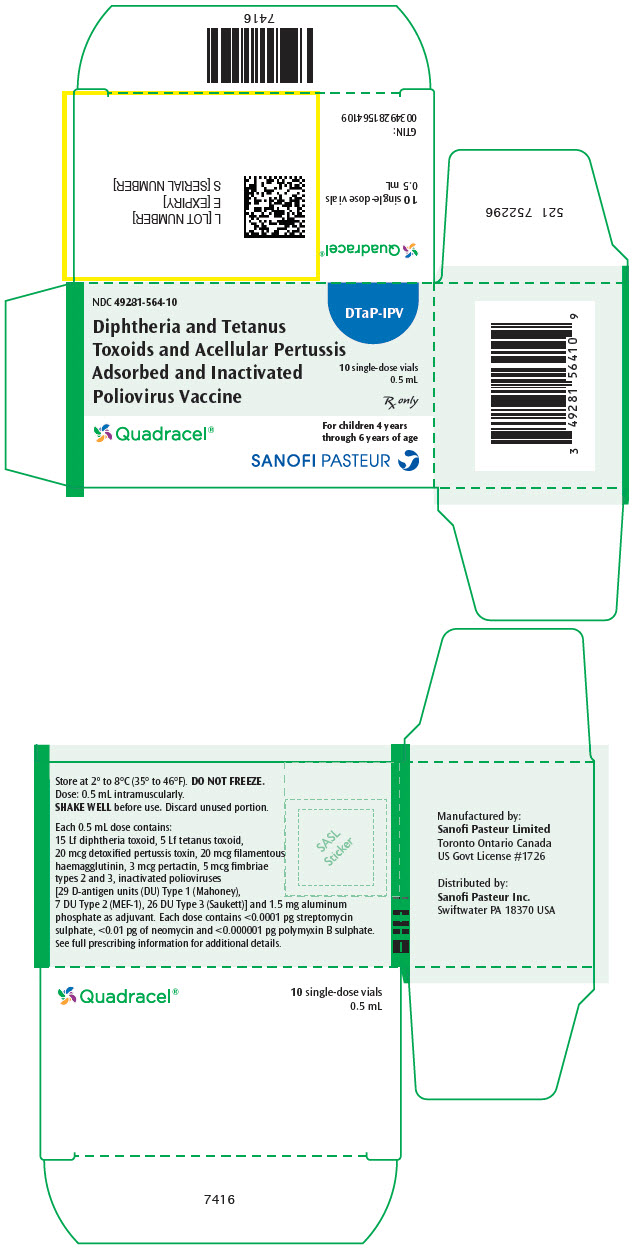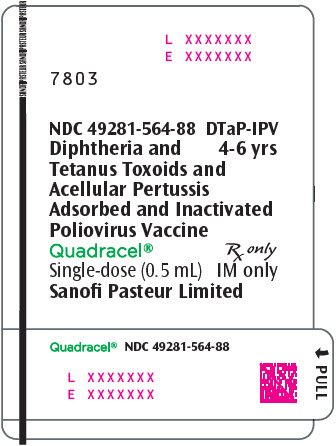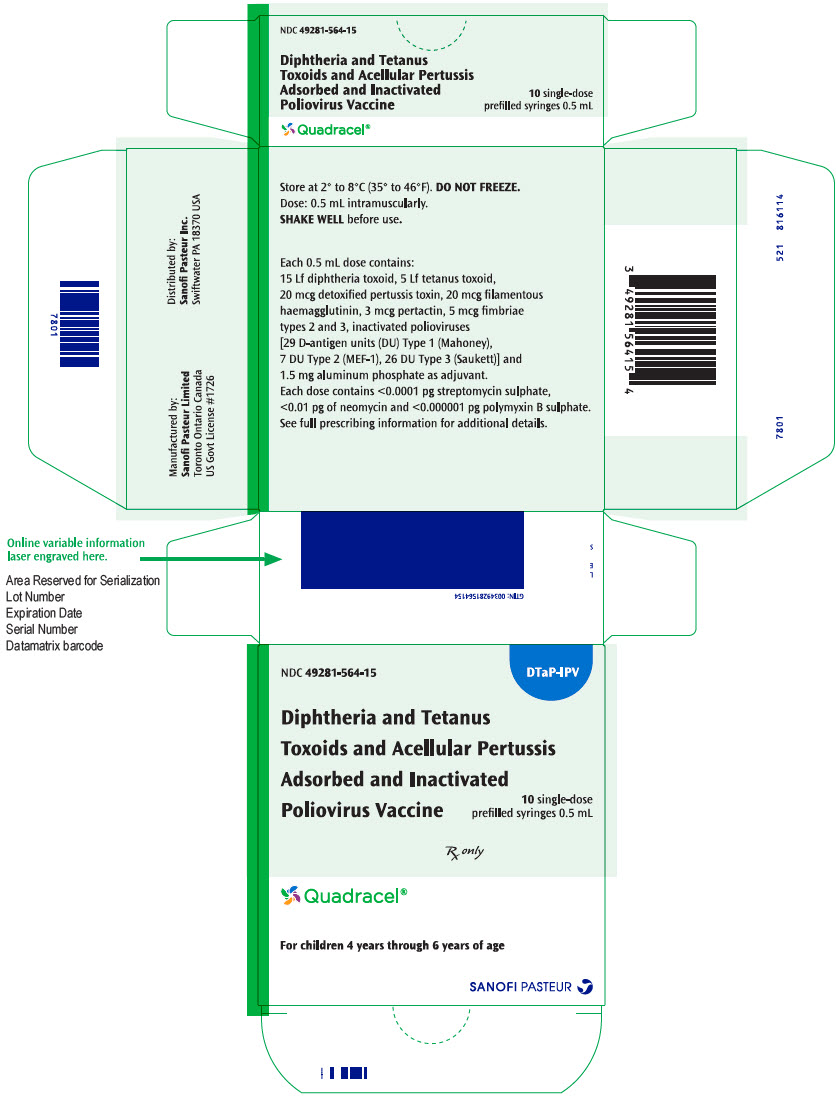 DRUG LABEL: QUADRACEL
NDC: 49281-564 | Form: INJECTION, SUSPENSION
Manufacturer: Sanofi Pasteur Inc.
Category: other | Type: VACCINE LABEL
Date: 20251113

ACTIVE INGREDIENTS: CORYNEBACTERIUM DIPHTHERIAE TOXOID ANTIGEN (FORMALDEHYDE INACTIVATED) 15 [Lf]/0.5 mL; CLOSTRIDIUM TETANI TOXOID ANTIGEN (FORMALDEHYDE INACTIVATED) 5 [Lf]/0.5 mL; BORDETELLA PERTUSSIS TOXOID ANTIGEN (GLUTARALDEHYDE INACTIVATED) 20 ug/0.5 mL; BORDETELLA PERTUSSIS FILAMENTOUS HEMAGGLUTININ ANTIGEN (FORMALDEHYDE INACTIVATED) 20 ug/0.5 mL; BORDETELLA PERTUSSIS PERTACTIN ANTIGEN 3 ug/0.5 mL; BORDETELLA PERTUSSIS FIMBRIAE 2/3 ANTIGEN 5 ug/0.5 mL; POLIOVIRUS TYPE 1 ANTIGEN (FORMALDEHYDE INACTIVATED) 29 [D'ag'U]/0.5 mL; POLIOVIRUS TYPE 2 ANTIGEN (FORMALDEHYDE INACTIVATED) 7 [D'ag'U]/0.5 mL; POLIOVIRUS TYPE 3 ANTIGEN (FORMALDEHYDE INACTIVATED) 26 [D'ag'U]/0.5 mL
INACTIVE INGREDIENTS: ALUMINUM PHOSPHATE 1.5 mg/0.5 mL; PHENOXYETHANOL 3.3 mg/0.5 mL; POLYSORBATE 80; FORMALDEHYDE; GLUTARAL; ALBUMIN BOVINE; STREPTOMYCIN SULFATE; NEOMYCIN; POLYMYXIN B SULFATE; WATER

HIGHLIGHTS OF PRESCRIBING INFORMATION

These highlights do not include all the information needed to use Quadracel safely and effectively. See full prescribing information for Quadracel.
Quadracel (Diphtheria and Tetanus Toxoids and Acellular Pertussis Adsorbed and Inactivated Poliovirus Vaccine)
Suspension for Intramuscular Injection
Initial U.S. Approval: 2015

1 INDICATIONS AND USAGE

Quadracel is a vaccine indicated for active immunization against diphtheria, tetanus, pertussis and poliomyelitis. A single dose of Quadracel is approved as a fifth dose in the diphtheria, tetanus, pertussis (DTaP) vaccination series, and as a fourth or fifth dose in the inactivated poliovirus (IPV) vaccination series in children 4 through 6 years of age whose previous DTaP vaccine doses have been with Pentacel, DAPTACEL and/or VAXELIS. (1)

2 DOSAGE AND ADMINISTRATION

A single intramuscular injection of 0.5 mL. (2)

3 DOSAGE FORMS AND STRENGTHS

Quadracel is a suspension for injection available in 0.5 mL single-dose vials and prefilled syringes. (3)

4 CONTRAINDICATIONS

- Severe allergic reaction (e.g., anaphylaxis) to any ingredient of Quadracel, or following any diphtheria toxoid, tetanus toxoid, pertussis-containing vaccine or inactivated poliovirus vaccine. (4.1) (11)
- Encephalopathy within 7 days of a previous pertussis-containing vaccine with no other identifiable cause. (4.2)
- Progressive neurologic disorder until a treatment regimen has been established and the condition has stabilized. (4.3)

5 WARNINGS AND PRECAUTIONS

- Carefully consider benefits and risks before administering Quadracel to persons with a history of:
  - fever ≥40.5°C (≥105°F), hypotonic-hyporesponsive episode (HHE) or persistent, inconsolable crying lasting ≥3 hours within 48 hours after a previous pertussis-containing vaccine. (5.2)
  - seizures within 3 days after a previous pertussis-containing vaccine. (5.2)
- If Guillain-Barré syndrome occurred within 6 weeks of receipt of a prior vaccine containing tetanus toxoid, the decision to give any tetanus toxoid-containing vaccine, including Quadracel, should be based on careful consideration of the potential benefits and possible risks. (5.3)

6 ADVERSE REACTIONS

In a clinical study, the most common solicited injection site reactions were pain (>75%), increase in arm circumference (>65%), erythema (>55%), and swelling (>40%). Common solicited systemic reactions were myalgia (>50%), malaise (>35%), and headache (>15%). (6.1)

To report SUSPECTED ADVERSE REACTIONS, contact Pharmacovigilance Department, Sanofi Pasteur Inc., Discovery Drive, Swiftwater, PA 18370 at 1-800-822-2463 (1-800-VACCINE) or VAERS at 1-800-822-7967 or http://vaers.hhs.gov

FULL PRESCRIBING INFORMATION

1 INDICATIONS AND USAGE

Quadracel® is a vaccine indicated for active immunization against diphtheria, tetanus, pertussis and poliomyelitis. A single dose of Quadracel is approved for use as a fifth dose in the diphtheria, tetanus, pertussis (DTaP) vaccination series, and as a fourth or fifth dose in the inactivated poliovirus (IPV) vaccination series in children 4 through 6 years of age whose previous DTaP vaccine doses have been with Pentacel® [Diphtheria and Tetanus Toxoids and Acellular Pertussis Vaccine Adsorbed, Inactivated Poliovirus and Haemophilus b conjugate (Tetanus Toxoid Conjugate) Vaccine], DAPTACEL® (Diphtheria and Tetanus Toxoids and Acellular Pertussis Vaccine Adsorbed) and/or VAXELIS (Diphtheria and Tetanus Toxoids and Acellular Pertussis, Inactivated Poliovirus, Haemophilus b Conjugate and Hepatitis B Vaccine).

2 DOSAGE AND ADMINISTRATION

For intramuscular injection only.

Just before use, shake the vial or syringe well, until a uniform, white, cloudy suspension results. Parenteral drug products should be inspected visually for particulate matter and discoloration prior to administration, whenever solution and container permit. If either of these conditions exist, the product should not be administered.

Administer a 0.5 mL dose of Quadracel vaccine intramuscularly into the deltoid muscle of the upper arm. Discard unused portion in vial.

Quadracel should not be combined through reconstitution or mixed with any other vaccine.

3 DOSAGE FORMS AND STRENGTHS

Quadracel is a suspension for injection available in 0.5 mL single-dose vials and prefilled syringes [see How Supplied/Storage and Handling (16)].

4 CONTRAINDICATIONS

4.1 Hypersensitivity

Severe allergic reaction (e.g., anaphylaxis) to any ingredient of Quadracel [see Description (11)] or following any diphtheria toxoid, tetanus toxoid, pertussis-containing vaccine, or inactivated poliovirus vaccine, is a contraindication to administration of Quadracel.

4.2 Encephalopathy

Encephalopathy (e.g., coma, decreased level of consciousness, prolonged seizures) within 7 days of a previous dose of a pertussis-containing vaccine that is not attributable to another identifiable cause is a contraindication to administration of any pertussis-containing vaccine, including Quadracel.

4.3 Progressive Neurologic Disorder

Progressive neurologic disorder, including infantile spasms, uncontrolled epilepsy, or progressive encephalopathy is a contraindication to administration of any pertussis-containing vaccine including Quadracel. Pertussis vaccine should not be administered to individuals with such conditions until a treatment regimen has been established and the condition has stabilized.

5 WARNINGS AND PRECAUTIONS

5.1 Management of Acute Allergic Reactions

Epinephrine hydrochloride solution (1:1,000) and other appropriate agents and equipment must be available for immediate use in case an anaphylactic or acute hypersensitivity reaction occurs.

5.2 Adverse Reactions Following Prior Pertussis Vaccination

If any of the following events have occurred within the specified period after administration of a pertussis vaccine, the decision to administer Quadracel should be based on careful consideration of benefits and risks.

- Temperature of ≥40.5°C (≥105°F) within 48 hours, not attributable to another identifiable cause.
- Collapse or shock-like state (hypotonic-hyporesponsive episode [HHE]) within 48 hours.
- Persistent, inconsolable crying lasting ≥3 hours within 48 hours.
- Seizures with or without fever within 3 days.

5.3 Guillain-Barré Syndrome

If Guillain-Barré syndrome occurred within 6 weeks of receipt of a prior vaccine containing tetanus toxoid, the decision to give any vaccine containing tetanus toxoid, including Quadracel, should be based on careful consideration of the potential benefits and possible risks.

5.4 Limitations of Vaccine Effectiveness

Vaccination with Quadracel may not protect all individuals.

5.5 Altered Immunocompetence

If Quadracel is administered to immunocompromised persons, including persons receiving immunosuppressive therapy, the expected immune response may not be obtained [see Drug Interactions (7.2)].

5.6 Syncope

Syncope (fainting) may occur in association with administration of injectable vaccines including Quadracel. Procedures should be in place to avoid injury from fainting.

6 ADVERSE REACTIONS

In a clinical study, the most common solicited injection site reactions were pain (>75%), increase in arm circumference (>65%), erythema (>55%), and swelling (>40%). Common solicited systemic reactions were myalgia (>50%), malaise (>35%), and headache (>15%).

6.1 Clinical Trials Experience

Because clinical trials are conducted under widely varying conditions, adverse reaction rates observed in the clinical trials of a vaccine cannot be directly compared to rates in the clinical trials of another vaccine and may not reflect the rates observed in practice. The adverse reaction information from clinical trials does, however, provide a basis for identifying the adverse events that appear to be related to vaccine use and for approximating rates of those events. The poliovirus component (poliovirus types 1, 2, and 3) of this formulation of Quadracel is grown in Vero cells [see Description (11)]. The clinical study data in this section were accrued with a Quadracel formulation in which poliovirus component was grown in MRC-5 cells.

In a randomized, controlled, multicenter study conducted in the US and Puerto Rico (Study M5I02; ClinicalTrials.gov Identifier: NCT01346293), 3,372 children, 4 to 6 years of age, who had received 4 doses of DAPTACEL and/or Pentacel vaccine(s) received Quadracel, or DAPTACEL + IPOL (Poliovirus Vaccine Inactivated) vaccines administered concomitantly but at separate sites. Subjects also received Measles, Mumps, and Rubella Virus Vaccine Live (MMR) (Merck & Co., Inc.) and Varicella Virus Vaccine Live (Varicella vaccine) (Merck & Co., Inc.) administered concomitantly at separate sites. Safety was evaluated in 2,733 subjects who received Quadracel and 621 subjects who received DAPTACEL + IPOL vaccines.

Among these subjects, 51.5% were male, 48.5% were female, 75.7% were Caucasian, 8.6% were Black, 7.9% were Hispanic, 0.9% were Asian, and 7.8% were of other racial/ethnic groups. The mean age for both groups was 4.4 years and the ratio of male to female subjects and ethnicity were balanced between both groups.

Solicited injection site reactions and systemic reactions were collected daily for 7 days following vaccination, via diary cards. Participants were monitored for unsolicited adverse events for 28 days and serious adverse events (SAEs) for 6 months after vaccination.

Solicited Adverse Reactions

The incidence and severity of solicited injection site and systemic adverse reactions that occurred within 7 days after vaccination in each study group are shown in Table 1.

Table 1: Percentage of Children 4 through 6 years of Age with Solicited Adverse Reactions by Intensity Within 7 Days of Vaccination with Quadracel or Concomitant but Separate DAPTACEL and IPOL vaccines Co-Administered with MMR and Varicella Vaccines [ClinicalTrials.gov Identifier: NCT01346293.]
 | Quadracel (N [N = The number of subjects with available data.] = 2,500-2,689) | DAPTACEL + IPOL (N = 598-603)
Injection Site Reactions | Quadracel site | DAPTACEL or IPOL site
Pain [Grade 1: Easily tolerated, Grade 2: Sufficiently discomforting to interfere with normal behavior or activities, Grade 3: Incapacitating, unable to perform usual activities.] , Any | 77.4 | 76.5
Pain, Grade 1 | 56.4 | 54.9
Pain, Grade 2 | 19.0 | 18.6
Pain, Grade 3 | 2.0 | 3.0
Change in limb circumference [Grade 1: >0 to <25 mm increase over pre-vaccination measurement, Grade 2: ≥25 to ≤50 mm increase over pre-vaccination measurement, Grade 3: >50 mm increase over pre-vaccination measurement.] , Any | 68.1 | 65.1
Change in limb circumference, Grade 1 | 59.8 | 58.6
Change in limb circumference, Grade 2 | 8.2 | 6.5
Change in limb circumference, Grade 3 | 0.2 | 0.0
Erythema, Any | 59.1 | 53.4
Erythema, >0 to <25 mm | 31.6 | 31.8
Erythema, ≥25 to <50 mm | 9.5 | 9.6
Erythema, ≥50 mm | 18.0 | 11.9
Swelling, Any | 40.2 | 36.4
Swelling, >0 to <25 mm | 23.5 | 23.1
Swelling, ≥25 to <50 mm | 8.1 | 6.1
Swelling, ≥50 mm | 8.6 | 7.1
Extensive limb swelling [Swelling of the injected limb including the adjacent joint (i.e., elbow and/or shoulder) as compared to baseline.] , Any | 1.5 | 1.3
Systemic Reactions
Myalgia [Grade 1: No interference with activity, Grade 2: Some interference with activity, Grade 3: Significant; prevents daily activity.] , Any | 53.8 | 52.6
Myalgia, Grade 1 | 36.0 | 33.5
Myalgia, Grade 2 | 15.8 | 16.3
Myalgia, Grade 3 | 1.9 | 2.8
Malaise, Any | 35.0 | 33.2
Malaise, Grade 1 | 21.7 | 18.7
Malaise, Grade 2 | 10.6 | 11.1
Malaise, Grade 3 | 2.6 | 3.3
Headache, Any | 15.6 | 16.6
Headache, Grade 1 | 11.9 | 11.9
Headache, Grade 2 | 3.1 | 4.0
Headache, Grade 3 | 0.6 | 0.7
Fever, Any | 6.0 | 6.9
Fever ≥38.0°C to ≤38.4°C | 2.6 | 3.0
Fever, ≥38.5°C to ≤38.9°C | 2.1 | 1.8
Fever, ≥39.0°C | 1.3 | 2.0

Serious Adverse Events

In Study M5I02, within 28 days following vaccination with Quadracel, or DAPTACEL + IPOL vaccines, and concomitant MMR and varicella vaccines, 0.1% of subjects (3/2,733) in the Quadracel group experienced a serious adverse event. During the same time period, 0.2% subjects (1/621) in the DAPTACEL + IPOL group experienced a SAE. Within the 6-month follow-up period after vaccination, SAEs were reported in 0.8% of subjects (21/2,733) who received Quadracel and 0.5% of subjects (3/621) who received DAPTACEL + IPOL vaccines, none of which were assessed as related to vaccination.

6.2 Postmarketing Experience

The following adverse events have been spontaneously reported, during the post-marketing use of Quadracel outside the US, in infants and children from 2 months through 6 years of age. Because these events are reported voluntarily from a population of uncertain size, it is not possible to estimate their frequency reliably or establish a causal relationship to vaccine exposure. This list includes adverse events based on one or more of the following factors: severity, frequency of reporting, or strength of evidence for a causal relationship to Quadracel.

- Immune system disorders
  Anaphylactic reaction, hypersensitivity and allergic reactions (such as rash, urticaria, dyspnea)
- Psychiatric disorders
  Screaming
- Nervous system disorders
  Somnolence, convulsion, febrile convulsion, HHE, hypotonia
- Cardiac disorders
  Cyanosis
- Vascular disorders
  Pallor
- General disorders and administration site conditions
  Listlessness
  Injection site reactions (including inflammation, mass, sterile abscess, and edema)
  Large injection site reactions (>50 mm), including limb swelling which may extend from the injection site beyond one or both joints
- Infections and Infestations
  Injection site cellulitis, injection site abscess

7 DRUG INTERACTIONS

7.1 Concomitant Administration with Other Vaccines

In the US clinical trial, Study M5I02, Quadracel was administered concomitantly with one or more of the following US-licensed vaccines: MMR vaccine and varicella vaccine [see Adverse Reactions (6.1)].

When Quadracel is given at the same time as another injectable vaccine(s), the vaccines should be administered with different syringes and at different injection sites.

7.2 Immunosuppressive Treatments

Immunosuppressive therapies, including irradiation, antimetabolites, alkylating agents, cytotoxic drugs and corticosteroids (used in greater than physiologic doses), may reduce the immune response to Quadracel [see Warnings and Precautions (5.5)].

8 USE IN SPECIFIC POPULATIONS

8.4 Pediatric Use

The safety and effectiveness of Quadracel has not been established in children less than 4 years of age or children 7 through 16 years of age and is not approved for use in these age groups.

11 DESCRIPTION

Quadracel (Diphtheria and Tetanus Toxoids and Acellular Pertussis Adsorbed and Inactivated Poliovirus Vaccine) is a sterile suspension for intramuscular injection.

Each 0.5 mL dose is formulated to contain 15 Lf diphtheria toxoid, 5 Lf tetanus toxoid, acellular pertussis antigens [20 mcg detoxified pertussis toxin (PT), 20 mcg filamentous hemagglutinin (FHA), 3 mcg pertactin (PRN), 5 mcg fimbriae types 2 and 3 (FIM)], and inactivated polioviruses [29 D-antigen units (DU) Type 1 (Mahoney), 7 DU Type 2 (MEF-1), 26 DU Type 3 (Saukett)].

Corynebacterium diphtheriae is grown in modified Mueller's growth medium. (1) After purification by ammonium sulfate fractionation, the diphtheria toxin is detoxified with formaldehyde and diafiltered.

Clostridium tetani is grown in modified Mueller-Miller casamino acid medium without beef heart infusion. (2) Tetanus toxin is detoxified with formaldehyde and purified by ammonium sulfate fractionation and diafiltration. Diphtheria and tetanus toxoids are individually adsorbed onto aluminum phosphate.

The acellular pertussis vaccine antigens are produced from Bordetella pertussis cultures grown in Stainer-Scholte medium (3) modified by the addition of casamino acids and dimethyl-beta-cyclodextrin. PT, FHA and PRN are isolated separately from the supernatant culture medium. FIM are extracted and copurified from the bacterial cells. The pertussis antigens are purified by sequential filtration, salt-precipitation, ultrafiltration and chromatography. PT is detoxified with glutaraldehyde. FHA is treated with formaldehyde and the residual aldehydes are removed by ultrafiltration. The individual antigens are adsorbed separately onto aluminum phosphate.

The Type 1, Type 2, and Type 3 polioviruses are individually grown in Vero cells (a continuous line of monkey kidney cells). Prior to viral propagation, the cells are grown in Iscove's medium, supplemented with calf serum. For viral propagation, the culture medium is replaced by M199 medium without calf serum. The viral harvests are concentrated and purified, then inactivated with formaldehyde to produce monovalent suspensions of each serotype. Specified quantities of monovalent suspensions of each serotype are mixed to produce the trivalent poliovirus concentrate. The adsorbed diphtheria, tetanus and acellular pertussis antigens are combined with aluminum phosphate, 2-phenoxyethanol (not as a preservative) and water for injection, into an intermediate concentrate. The trivalent poliovirus concentrate is added and the vaccine is diluted to its final concentration.

Each 0.5 mL dose contains 1.5 mg aluminum phosphate (0.33 mg aluminum) as the adjuvant, <8.1 mcg polysorbate 80, 3.3 mg (0.6% v/v) 2-phenoxyethanol (not as a preservative), 2 mcg to 7 mcg residual formaldehyde, <50 ng residual glutaraldehyde, ≤10 ng residual bovine serum albumin, <0.0001 pg streptomycin sulphate, <0.01 pg of neomycin and <0.000001 pg polymyxin B sulphate.

Quadracel does not contain a preservative.

Both diphtheria and tetanus toxoids induce at least 2 neutralizing units per mL in the guinea pig potency test. The potency of the acellular pertussis antigens is evaluated by the antibody response of immunized mice to detoxified PT, FHA and FIM as measured by enzyme-linked immunosorbent assay (ELISA). The potency of the PRN component of acellular pertussis antigens is measured by in vitro PRN antigenicity ELISA. The potency of the inactivated poliovirus antigens is determined by using the in vitro D-Antigen ELISA for each serotype..

12 CLINICAL PHARMACOLOGY

12.1 Mechanism of Action

Diphtheria

Diphtheria is an acute toxin-mediated disease caused by toxigenic strains of C. diphtheriae. Protection against disease is due to the development of neutralizing antibodies to diphtheria toxin. A serum diphtheria antitoxin level of 0.01 IU/mL is the lowest level giving some degree of protection. Antitoxin levels of at least 0.1 IU/mL are generally regarded as protective. (4) Levels of 1.0 IU/mL have been associated with long-term protection. (5)

Tetanus

Tetanus is an acute disease caused by an extremely potent neurotoxin produced by C. tetani. Protection against disease is due to the development of neutralizing antibodies to tetanus toxin. A serum tetanus antitoxin level of at least 0.01 IU/mL, measured by neutralization assay, is considered the minimum protective level. (4) (6). A tetanus antitoxoid level ≥0.1 IU/mL as measured by the ELISA used in clinical studies of Quadracel is considered protective.

Pertussis

Pertussis (whooping cough) is a respiratory disease caused by B. pertussis. This Gram-negative coccobacillus produces a variety of biologically active components, though their role in either the pathogenesis of, or immunity to, pertussis has not been clearly defined.

There is no well-established serological correlate of protection for pertussis. Because DAPTACEL contains the same pertussis antigens manufactured by the same process as those in Quadracel, the effectiveness of Quadracel against pertussis was based on a comparison of pertussis immune responses following Quadracel to those following DAPTACEL (Diphtheria and Tetanus Toxoids and Acellular Pertussis Vaccine Adsorbed) [see Clinical Studies (14)]. The efficacy of the pertussis component of DAPTACEL was determined in clinical trials of DAPTACEL administered to infants (see DAPTACEL prescribing information). Quadracel contains twice as much detoxified PT and four times as much FHA as DAPTACEL. Quadracel contains the same quantity of the same pertussis antigens manufactured by the same process as those in Pentacel and VAXELIS.

Poliomyelitis

Polioviruses, of which there are three serotypes (Types 1, 2, and 3), are enteroviruses. The presence of poliovirus type-specific neutralizing antibodies has been correlated with protection against poliomyelitis. (7)

13 NONCLINICAL TOXICOLOGY

13.1 Carcinogenesis, Mutagenesis, Impairment of Fertility

Quadracel has not been evaluated for carcinogenic or mutagenic potential or impairment of fertility.

14 CLINICAL STUDIES

The poliovirus component (poliovirus types 1, 2 and 3) of this formulation of Quadracel is grown in Vero cells [see Description (11)]. The clinical study data in this section were accrued with a Quadracel formulation in which the poliovirus component was grown in MRC-5 cells. The poliovirus component of the two formulations of Quadracel are analytically comparable.

14.1 Immunogenicity

In Study M5I02, children 4 through 6 years of age received Quadracel or DAPTACEL + IPOL as the fifth dose in the diphtheria, tetanus, and pertussis vaccination series and the fourth or fifth dose in the inactivated poliovirus vaccination series. Subjects also received their second dose of MMR and Varicella vaccines, concomitantly. The immunogenicity subset comprised 263 subjects in the Quadracel group and 253 subjects in the DAPTACEL + IPOL vaccines group [see Clinical Trials Experience (6.1)].

Antibody levels to diphtheria, tetanus, pertussis (PT, FHA, PRN and FIM) and poliovirus antigens were measured in sera obtained immediately prior to vaccination and 28 days after vaccination. The co-primary endpoints were booster response rates and antibody geometric mean concentrations/titers (GMCs/GMTs) to diphtheria, tetanus, pertussis and poliovirus antigens elicited after vaccination. Booster response rates and antibody GMCs/GMTs following Quadracel vaccination were compared to those after DAPTACEL + IPOL vaccination.

Quadracel was non-inferior to DAPTACEL + IPOL vaccines administered concomitantly at separate sites, as demonstrated by comparison of the post-vaccination antibody booster response rates and GMCs/GMTs to diphtheria and tetanus (Table 2), to all pertussis antigens (Table 3) and to poliovirus 1, 2 and 3 (Table 4).

Table 2: Booster Response Rates, Pre- and Post-Vaccination Seroprotection Rates and Post-Vaccination Antibody Levels to Diphtheria and Tetanus Antigens Following Quadracel or Concomitant but Separate DAPTACEL and IPOL Vaccines Co-Administered with MMR and Varicella Vaccines [ClinicalTrials.gov Identifier: NCT01346293.]
 | Quadracel (N [N = The number of subjects with available data.] =253-262) | DAPTACEL + IPOL (N=248-253)
Anti-Diphtheria
% Booster Response [Booster response: In subjects with pre-vaccination antibody concentrations <0.1 IU/mL, a post-vaccination level ≥0.4 IU/mL; in subjects with pre-vaccination antibody concentrations ≥0.1 IU/mL but <2.0 IU/mL, a 4-fold rise in post-vaccination level; in subjects with pre-vaccination antibody level ≥2.0 IU/mL, a 2-fold rise in post-vaccination level.] | 97.3 [Quadracel was non-inferior to DAPTACEL + IPOL based on the post-vaccination booster response rates for diphtheria and tetanus (lower limits of the 2-sided 95% CIs of the difference [Quadracel minus DAPTACEL + IPOL] were >-10%).] | 99.2
Pre-vaccination % ≥0.1 IU/mL [Seroprotection: anti-diphtheria and anti-tetanus antibody concentrations ≥ 0.1 IU/mL and ≥ 1.0 IU/mL.] | 90.7 | 83.1
Post-vaccination % ≥0.1 IU/mL | 100.0 | 99.6
Post-vaccination % ≥1.0 IU/mL | 99.6 | 99.6
Post-vaccination GMC (IU/mL) | 18.6 [Quadracel was non-inferior to DAPTACEL + IPOL based on the post-vaccination GMCs for diphtheria and tetanus (lower limits of the 2-sided 95% CIs of the ratio [Quadracel / DAPTACEL + IPOL] were >2/3).] | 15.5
Anti-Tetanus
% Booster Response | 84.2 | 84.3
Pre-vaccination % ≥0.1 IU/mL | 91.7 | 89.1
Post-vaccination % ≥0.1 IU/mL | 100.0 | 99.2
Post-vaccination % ≥1.0 IU/mL | 98.9 | 96.8
Post-vaccination GMC (IU/mL) | 6.4 | 5.5

Table 3: Booster Response Rates and Post-vaccination Antibody Levels to Pertussis Antigens Following Quadracel or Concomitant but Separate DAPTACEL and IPOL Vaccines Co-Administered with MMR and Varicella Vaccines [ClinicalTrials.gov Identifier: NCT01346293.]
 | Quadracel (N [N = The number of subjects with available data.] =250-255) | DAPTACEL + IPOL (N=247-249)
Anti-PT
% Booster Response [Booster response: In subjects with pre-vaccination antibody concentrations <LLOQ, a post-vaccination level ≥4×LLOQ; in subjects with pre-vaccination antibody concentrations ≥LLOQ but <4×LLOQ, a 4-fold rise in post-vaccination level; in subjects with pre-vaccination antibody level ≥4×LLOQ, a 2-fold rise in post-vaccination level.] | 95.2 [Quadracel was non-inferior to DAPTACEL + IPOL based on the post-vaccination booster response rates for all pertussis antigens (lower limits of the 2-sided 95% CIs of the difference [Quadracel minus DAPTACEL + IPOL] were > -10%).] | 89.9
Post-vaccination GMC (EU/mL) | 120.7 [Quadracel was non-inferior to DAPTACEL + IPOL based on the post-vaccination GMCs for all pertussis antigens (lower limits of the 2-sided 95% CIs of the ratio [DTaP-IPV / DAPTACEL + IPOL] were >2/3).] | 61.3
Anti-FHA
% Booster Response | 94.9 | 87.5
Post-vaccination GMC (EU/mL) | 123.5 | 79.0
Anti-PRN
% Booster Response | 96.9 | 93.1
Post-vaccination GMC (EU/mL) | 282.6 | 187.5
Anti-FIM
% Booster Response | 97.2 | 92.4
Post-vaccination GMC (EU/mL) | 505.8 | 378.9

Table 4: Booster Response Rates, Pre- and Post-Vaccination Seroprotection Rates and Post-vaccination Antibody Levels to Poliovirus Antigens Following Quadracel or Concomitant but Separate DAPTACEL and IPOL Vaccines Co-Administered with MMR and Varicella Vaccines [ClinicalTrials.gov Identifier: NCT01346293.]
 | Quadracel (N [N = The number of subjects with available data.] =247-258) | DAPTACEL + IPOL (N=248-253)
Anti-Poliovirus 1
% Booster Response [Booster response: In subjects with pre-vaccination antibody concentrations <1:8 dilution, post-vaccination levels ≥1:8 dil; in subjects with pre-vaccination antibody concentrations ≥1:8 dilution, a 4-fold rise in post-vaccination antibody levels.] | 85.9 [Quadracel was non-inferior to DAPTACEL + IPOL based on the post-vaccination booster response rates for polio types 1, 2 and 3 (lower limits of the 2-sided 95% CIs of the difference [Quadracel minus DAPTACEL + IPOL] were > -10%).] | 82.3
Pre-vaccination % ≥1:8 dilution | 98.4 | 98.8
Post-vaccination % ≥1:8 dilution | 100.0 | 99.6
Post-vaccination GMT | 3,477 [Quadracel was non-inferior to DAPTACEL + IPOL based on the post-vaccination GMTs for polio types 1, 2 and 3 (lower limits of the 2-sided 95% CIs of the ratio [Quadracel / DAPTACEL + IPOL] were >2/3).] | 2,731
Anti-Poliovirus 2
% Booster Response | 78.3 | 79.0
Pre-vaccination % ≥1:8 dilution | 99.6 | 99.6
Post-vaccination % ≥1:8 dilution | 100.0 | 100.0
Post-vaccination GMT | 3,491 | 3,894
Anti-Poliovirus 3
% Booster Response | 85.0 | 84.7
Pre-vaccination % ≥1:8 dilution | 96.8 | 93.1
Post-vaccination % ≥1:8 dilution | 100.0 | 100.0
Post-vaccination GMT | 4,591 | 3,419

15 REFERENCES

1 Stainer DW. Production of diphtheria toxin. In: Manclark CR, editor. Proceedings of an informal consultation on the World Health Organization requirements for diphtheria, tetanus, pertussis and combined vaccines. United States Public Health Service, Bethesda, MD. DHHS 91-1174. 1991:7-11.
2 Mueller JH, Miller PA. Variable factors influencing the production of tetanus toxin. J Bacteriol 1954;67(3):271-7.
3 Stainer DW, Scholte MJ. A simple chemically defined medium for the production of phase I Bordetella pertussis. J Gen Microbiol 1970;63:211-20.
4 Department of Health and Human Services, Food and Drug Administration. Biological products; bacterial vaccines and toxoids; implementation of efficacy review; proposed rule. Federal Register 1985;50(240):51002-117.
5 Vitek CR, Tiwari TSP, Wharton M. Diphtheria toxoid. In: Plotkin SA, Orenstein WA, and Offit PA, editors. Vaccines. 7th ed. Philadelphia, PA: WB Saunders; 2018;7:261-75.
6 Roper M, Wassilak SGF, Tiwari TSP, Orenstein WA. Tetanus toxoid. In: Plotkin SA, Orenstein WA, and Offit PA, editors. Vaccines. 7th ed. Philadelphia, PA: WB Saunders; 2018;18:1052-79.
7 Sutter RW, et al. Defining surrogate serologic tests with respect to predicting protective vaccine efficacy: Poliovirus vaccination. In: Williams JC, et al. eds. Combined vaccines and simultaneous administration. Current issues and perspectives. New York, NY: The New York Academy of Sciences. 1995:289-99.

16 HOW SUPPLIED/STORAGE AND HANDLING

16.1 How Supplied

The vial stopper, syringe plunger stopper, and syringe tip cap are not made with natural rubber latex.

Single-dose vial (NDC No. 49281-564-58) in packages of 10 vials (NDC No. 49281-564-10).

Single-dose, prefilled syringe, without needle, (NDC No. 49281-564-88). Supplied as package of 10 (NDC No. 49281-564-15).

16.2 Storage and Handling

Quadracel should be stored at 2° to 8°C (35° to 46°F). Do not freeze. Product which has been exposed to freezing should not be used. Do not use after expiration date shown on the label.

17 PATIENT COUNSELING INFORMATION

Inform the parent or guardian of the following:

- The potential benefits and risks of immunization with Quadracel.
- The common adverse reactions that have occurred following administration of Quadracel or other vaccines containing similar components.
- Other adverse reactions can occur. Call healthcare provider with any adverse reactions of concern.

Provide the Vaccine Information Statements (VIS), which are required by the National Childhood Vaccine Injury Act of 1986.

Manufactured by:
Sanofi Pasteur Limited
Toronto Ontario Canada

Distributed by:
Sanofi Pasteur Inc.
Swiftwater PA 18370 USA

Quadracel® is a registered trademark of Sanofi, its affiliates and subsidiaries.

R4-1125 USA

PRINCIPAL DISPLAY PANEL - 0.5 mL Vial Label

NDC 49281-564-58
DTaP-IPV

Diphtheria and
Tetanus Toxoids and Acellular
Pertussis Adsorbed and
Inactivated Poliovirus Vaccine

4 – 6 yrs

Quadracel®
Rx only

Single-dose (0.5 mL)
IM only

Sanofi Pasteur Limited

PRINCIPAL DISPLAY PANEL - 0.5 mL Vial Package

NDC 49281-564-10

DTaP-IPV

Diphtheria and Tetanus
Toxoids and Acellular Pertussis
Adsorbed and Inactivated
Poliovirus Vaccine

10 single-dose vials
0.5 mL

Rx only

Quadracel®

For children 4 years
through 6 years of age

SANOFI PASTEUR

PRINCIPAL DISPLAY PANEL - 0.5 mL Syringe Label

L XXXXXXX
E XXXXXXX

7803

NDC 49281-564-88
DTaP-IPV
Diphtheria and
Tetanus Toxoids and
Acellular Pertussis
Adsorbed and Inactivated
Poliovirus Vaccine
Quadracel®
Rx only
Single-dose (0.5 mL)
IM only
Sanofi Pasteur Limited
4-6 yrs

Quadracel® NDC 49281-564-88

L XXXXXXX
E XXXXXXX

↓ PULL

PRINCIPAL DISPLAY PANEL - 0.5 mL Syringe Package

NDC 49281-564-15

DTaP-IPV

Diphtheria and Tetanus
Toxoids and Acellular Pertussis
Adsorbed and Inactivated
Poliovirus Vaccine
10 single-dose
prefilled syringes 0.5 mL

Rx only

Quadracel®

For children 4 years through 6 years of age

SANOFI PASTEUR